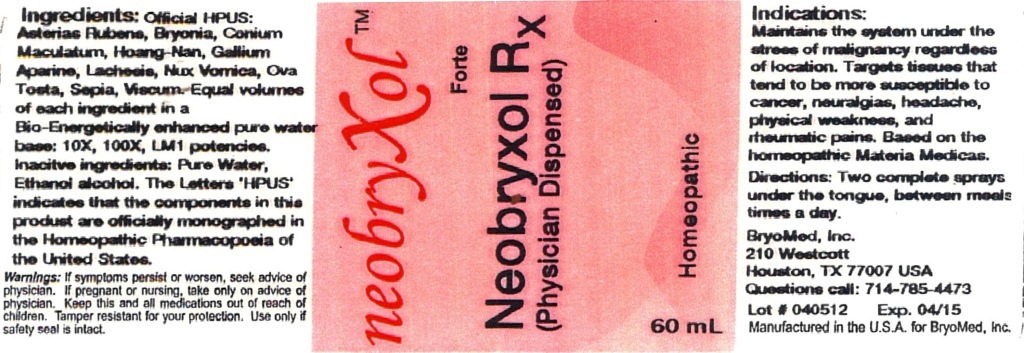 DRUG LABEL: NeobryXol Forte
NDC: 45984-0002 | Form: LIQUID
Manufacturer: Bryomed Inc.
Category: homeopathic | Type: HUMAN PRESCRIPTION DRUG LABEL
Date: 20120405

ACTIVE INGREDIENTS: ASTERIAS RUBENS 10 [hp_X]/30 mL; BRYONIA ALBA ROOT 10 [hp_X]/30 mL; CONIUM MACULATUM FLOWERING TOP 10 [hp_X]/30 mL; STRYCHNOS WALLICHIANA BARK 10 [hp_X]/30 mL; GALIUM APARINE 10 [hp_X]/30 mL; LACHESIS MUTA VENOM 10 [hp_X]/30 mL; STRYCHNOS NUX-VOMICA SEED 10 [hp_X]/30 mL; EGG SHELL, COOKED 10 [hp_X]/30 mL; SEPIA OFFICINALIS JUICE 10 [hp_X]/30 mL; VISCUM ALBUM WHOLE 10 [hp_X]/30 mL
INACTIVE INGREDIENTS: WATER; ALCOHOL

NeobryXol Forte

Active Ingredients

Official HPUS: Asterias rubens, Bryonia, Conium maculatum, Galium aparine, Hoang-nan, Lachesis mutus, Nux vomica, Ova tosta, Sepia and Viscum album.

Reference image forte.jpg

Inactive Ingredients

Equal volumes of each ingredient in a Bio-Energetically enhanced pure water base: 10X, 100X, LM1 potency. Inactive ingredients: pure water and alcohol.

Reference image forte.jpg

Purpose

Indication: maintains the system under the stress of malignancy regardless of location. Targets tissues that tend to be more susceptible to:

- cancer
- neuralgias
- dropsy of extremities
- yellowed skin
- headache
- physical weakness
- rheumatic pains

Based on the homeopathic Materia Medicas.
Reference image forte.jpg

Dosage and Administration

Directions: Two complete sprays under the tongue, between meals, 3 times a day.
Reference image forte.jpg

Warnings

Warnings: If symptoms persist or worsen, seek advice of physician. If pregnant or nursing, take only on advice of physician. Keep this and all medication out of reach of children. Tamper resistant for your protection. Use only if safety seal is intact.

Caution: Federal Law prohibits dispensing without prescription.

Reference image forte.jpg

KEEP OUT OF REACH OF CHILDREN

Keep this and all medication out of reach of children.

Reference image forte.jpg

Indications and Usage

Indication: Maintains the system under the stress of malignancy regardless of location. Targets tissues that tend to be more susceptible to cancer, neuralgias and dropsy of extremities, yellowed skin, headache, physical weakness and rheumatic pains.

Based on the homeopathic Materia Medicas.
Reference image forte.jpg

PACKAGE LABEL

Bryomed, Inc.

210 Westcott

Houston, TX 77007

Questions call 714-785-4473